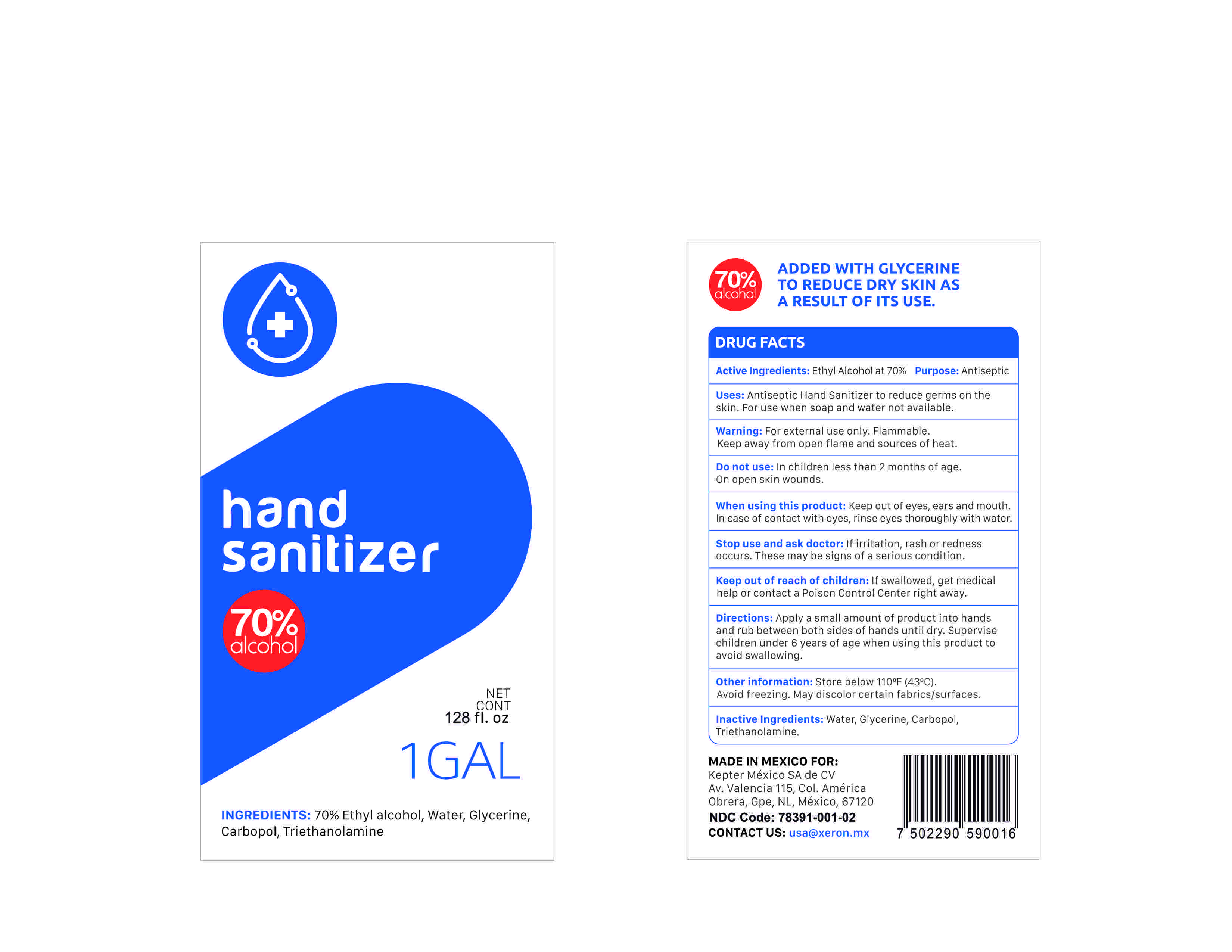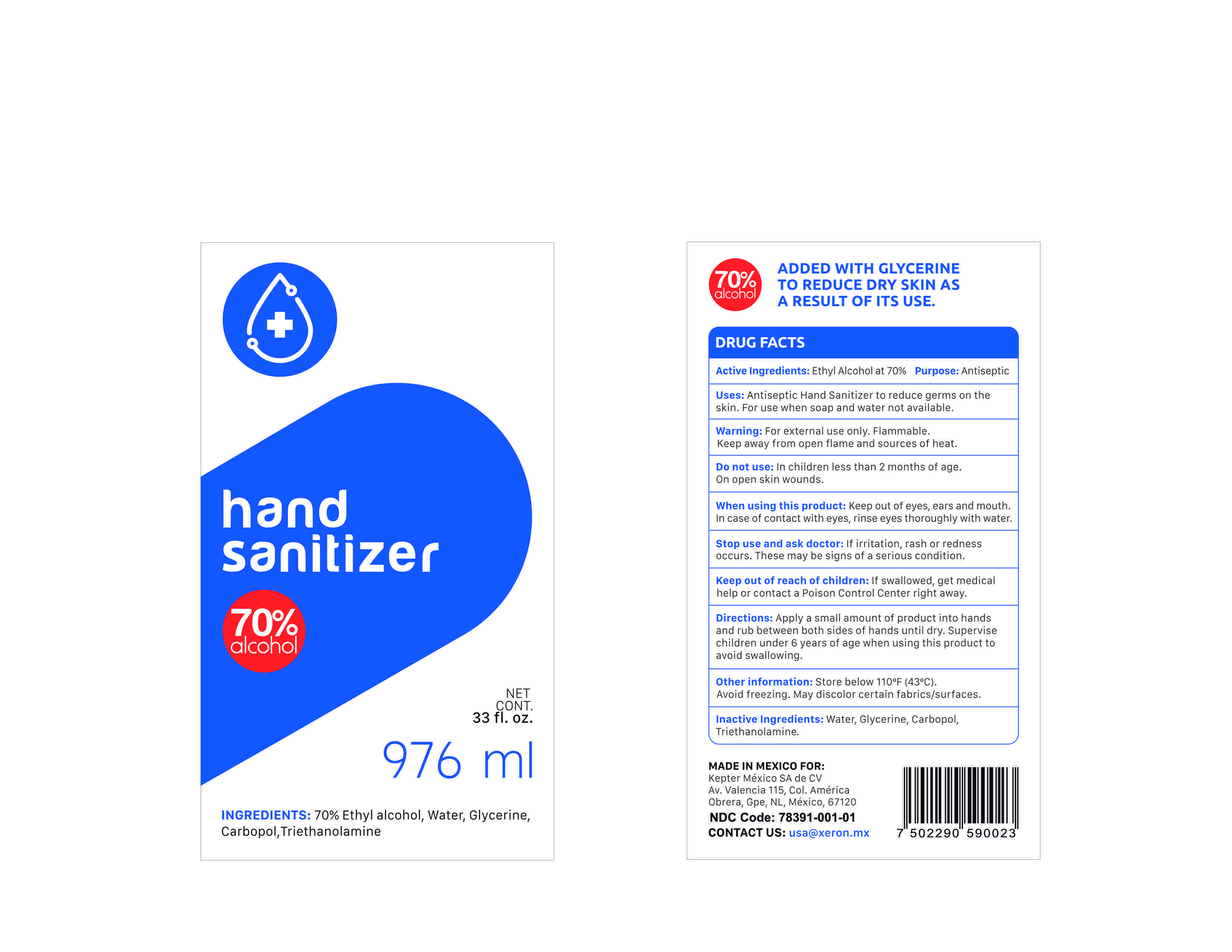 DRUG LABEL: Hand Sanitizer
NDC: 75432-003 | Form: GEL
Manufacturer: Medek, LLC
Category: otc | Type: HUMAN OTC DRUG LABEL
Date: 20200623

ACTIVE INGREDIENTS: ALCOHOL 70 mL/100 mL
INACTIVE INGREDIENTS: GLYCERIN 0.5 mL/100 mL; CARBOMER 940 0.5 mL/100 mL; WATER 28 mL/100 mL; TROLAMINE 0.4 mL/100 mL

Kepter Hand Sanitizer

This is a hand sanitizer manufactured using only the following United States Pharmacopoeia (USP) grade ingredients:

1. Alcohol (ethanol) (USP or Food Chemical Codex (FCC) grade) (70%, volume/volume (v/v)) in an aqueous solution denatured according to Alcohol and Tobacco Tax and Trade Bureau regulations in 27 CFR part 20.
2. Glycerol (.5% v/v).
3. Carbopol (0.5% v/v).
4. Triethanolamine (0.4% v/v)
5. Sterile distilled water or boiled cold water.

Active Ingredient(s)

Ethyl Alcohol 70% v/v. Purpose: Antiseptic

Purpose

Antiseptic, Hand Sanitizer

Use

Antiseptic Hand Sanitizer to reduce germs on skin. For use when soap and water are not available.

Warnings

For external use only. Flammable. Keep away from open flame and sources of heat.

Do not use

- in children less than 2 months of age
- on open skin wounds

When using this product keep out of eyes, ears, and mouth. In case of contact with eyes, rinse eyes thoroughly with water.
Stop use and ask a doctor if irritation, rash or redness occurs. These may be signs of a serious condition.
Keep out of reach of children. If swallowed, get medical help or contact a Poison Control Center right away.

Stop use and ask a doctor if irritation, rash or redness occurs. These may be signs of a serious condition.

Keep out of reach of children. If swallowed, get medical help or contact a Poison Control Center right away.

Directions

Apply a small amount of product into hands and rub between both sides of hands until dry. Supervise children under 6 years of age when using this product to avoid swallowing.

Other information

- Store below 110F (43C)
- Avoid freezing. May discolor certain fabrics/surfaces.

Inactive ingredients

Water, glycerin, carbopol, Triethanolamine.

Package Label - Principal Display Panel

976 mL NDC: 75432-003-01

3786 mL NDC: 75432-003-02